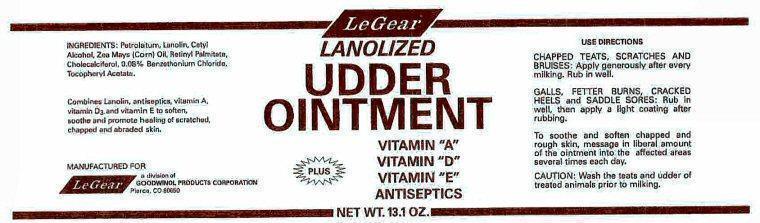 DRUG LABEL: LeGear Lanolized Udder
NDC: 42822-205 | Form: OINTMENT
Manufacturer: LeGear Animal Health
Category: animal | Type: OTC ANIMAL DRUG LABEL
Date: 20211101

ACTIVE INGREDIENTS: BENZETHONIUM CHLORIDE 1000 mg/1 g
INACTIVE INGREDIENTS: PETROLATUM; LANOLIN; CETYL ALCOHOL; CORN OIL; VITAMIN A PALMITATE; CHOLECALCIFEROL; .ALPHA.-TOCOPHEROL ACETATE

USE

CHAPPED TEATS, SCRATCHES AND BRUISES

GALLS, FETTER BURNS, CRACKED HEELS and SADDLE SORES

INGREDIENTS

INGREDIENTS: Lanolin, Petrolatum, Benzethonium Chloride, Cetyl Alcohol, Vitamins A, D3, and E.

Combines lanolin, antiseptics, vitamin A, vitamin D3, and vitamin E to soften, soothe and promote healing
of scratched, chapped and abraded skin.

DIRECTIONS

CHAPPED TEATS, SCRATCHES AND BRUISES: Apply generously after each milking. Rub in well.
GALLS, FETTER BURNS, CRACKED HEELS and SADDLE SORES: Rub in well, then apply a light coating after rubbing.
To soothe and soften chapped and rough skin, message in liberal amount of the ointment into the affected
areas several times each day.

CAUTION:

Wash the teats and udder of treated animals prior to milking.

Product Label

LeGear
LANOLIZED UDDER OINTMENT
VITAMIN "A"
VITAMIN "D" PLUS
VITAMIN "E"
ANTISEPTICS

MANUFACTURED FOR LeGear a division of GOODWINOL PRODUCTS CORPORATION Pierce, CO 80650
NET WT. 13.1 OZ

res